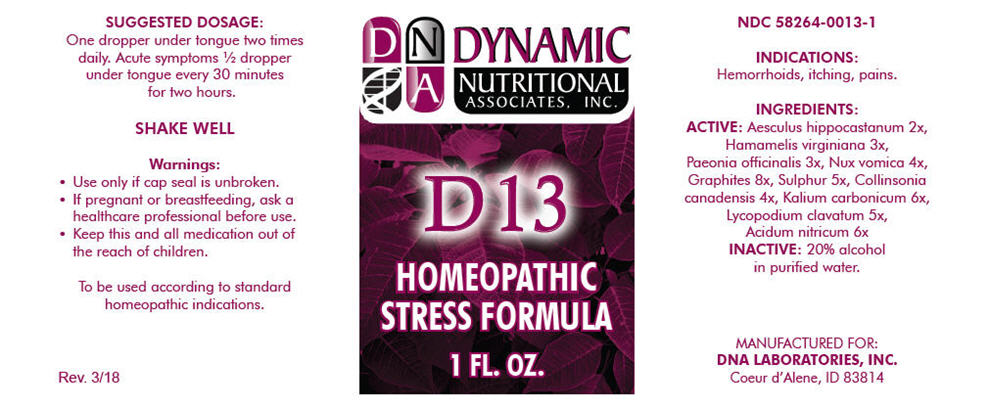 DRUG LABEL: D-13
NDC: 58264-0013 | Form: SOLUTION
Manufacturer: DNA Labs, Inc.
Category: homeopathic | Type: HUMAN OTC DRUG LABEL
Date: 20250113

ACTIVE INGREDIENTS: HORSE CHESTNUT 2 [hp_X]/1 mL; HAMAMELIS VIRGINIANA ROOT BARK/STEM BARK 3 [hp_X]/1 mL; PAEONIA OFFICINALIS ROOT 3 [hp_X]/1 mL; STRYCHNOS NUX-VOMICA SEED 4 [hp_X]/1 mL; GRAPHITE 8 [hp_X]/1 mL; SULFUR 5 [hp_X]/1 mL; COLLINSONIA CANADENSIS ROOT 4 [hp_X]/1 mL; POTASSIUM CARBONATE 6 [hp_X]/1 mL; LYCOPODIUM CLAVATUM SPORE 5 [hp_X]/1 mL; NITRIC ACID 6 [hp_X]/1 mL
INACTIVE INGREDIENTS: ALCOHOL; WATER

D-13

NDC 58264-0013-1

INDICATIONS

PURPOSE

Hemorrhoids, itching, pains.

INGREDIENTS

ACTIVE

Aesculus hippocastanum 2x, Hamamelis virginiana 3x, Paeonia officinalis 3x, Nux vomica 4x, Graphites 8x, Sulphur 5x, Collinsonia canadensis 4x, Kalium carbonicum 6x, Lycopodium clavatum 5x, Acidum nitricum 6x

INACTIVE

20% alcohol in purified water.

SUGGESTED DOSAGE

One dropper under tongue two times daily. Acute symptoms ½ dropper under tongue every 30 minutes for two hours.

STORAGE AND HANDLING

SHAKE WELL

Warnings

- Use only if cap seal is unbroken.

PREGNANCY OR BREAST FEEDING

- If pregnant or breastfeeding, ask a healthcare professional before use.

KEEP OUT OF REACH OF CHILDREN

- Keep this and all medication out of the reach of children.

To be used according to standard homeopathic indications.

PRINCIPAL DISPLAY PANEL - 1 FL. OZ. Bottle Label

DYNAMIC
NUTRITIONAL
ASSOCIATES, INC.

D 13

HOMEOPATHIC
STRESS FORMULA

1 FL. OZ.